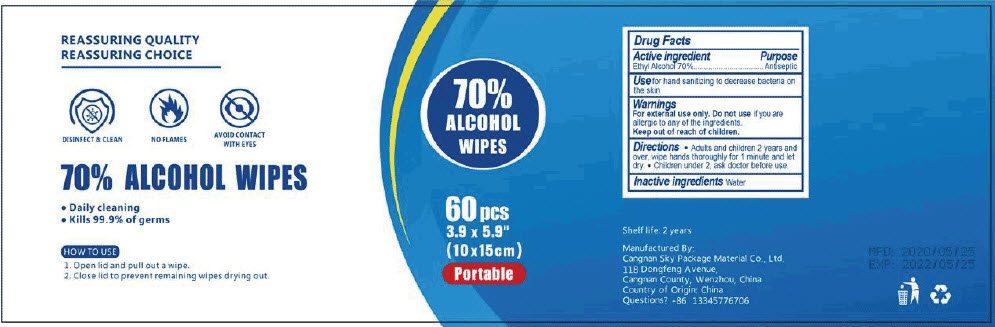 DRUG LABEL: 70 Percent Alcohol Wipes
NDC: 79118-100 | Form: CLOTH
Manufacturer: Wdb Trading, LLC
Category: otc | Type: HUMAN OTC DRUG LABEL
Date: 20200923

ACTIVE INGREDIENTS: ALCOHOL 70 mL/100 mL
INACTIVE INGREDIENTS: WATER

70% Alcohol Wipes

Drug Facts

Active ingredient

Ethyl Alcohol 70%

Purpose

Antiseptic

Use

for hand sanitizing to decrease bacteria on the skin

Warnings

For external use only. Do not use if you are allergic to any of the ingredients.

Keep out of reach of children.

Directions

- Adults and children 2 years and over, wipe hands thoroughly for 1 minute and let dry.
- Children under 2, ask doctor before use.

Inactive ingredients

Water

Questions?

+86 13345776706

Manufactured By:
Cangnan Sky Package Material Co., Ltd.
118 Dongfeng Avenue,
Cangnan County, Wenzhou, China

PRINCIPAL DISPLAY PANEL - 60 Count Container Label

70%
ALCOHOL
WIPES

60 pcs
3.9 x 5.9"
(10 x 15cm)
Portable